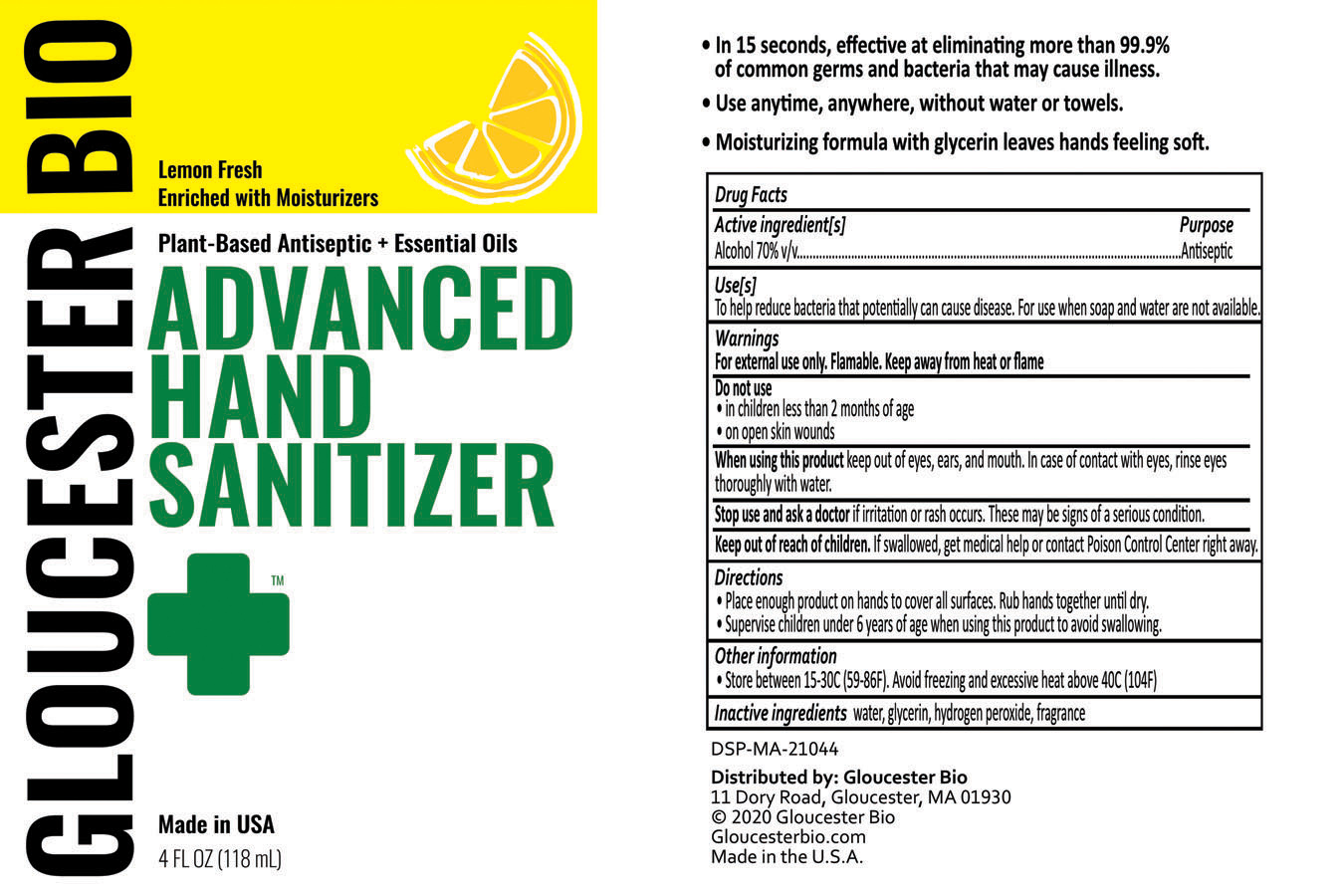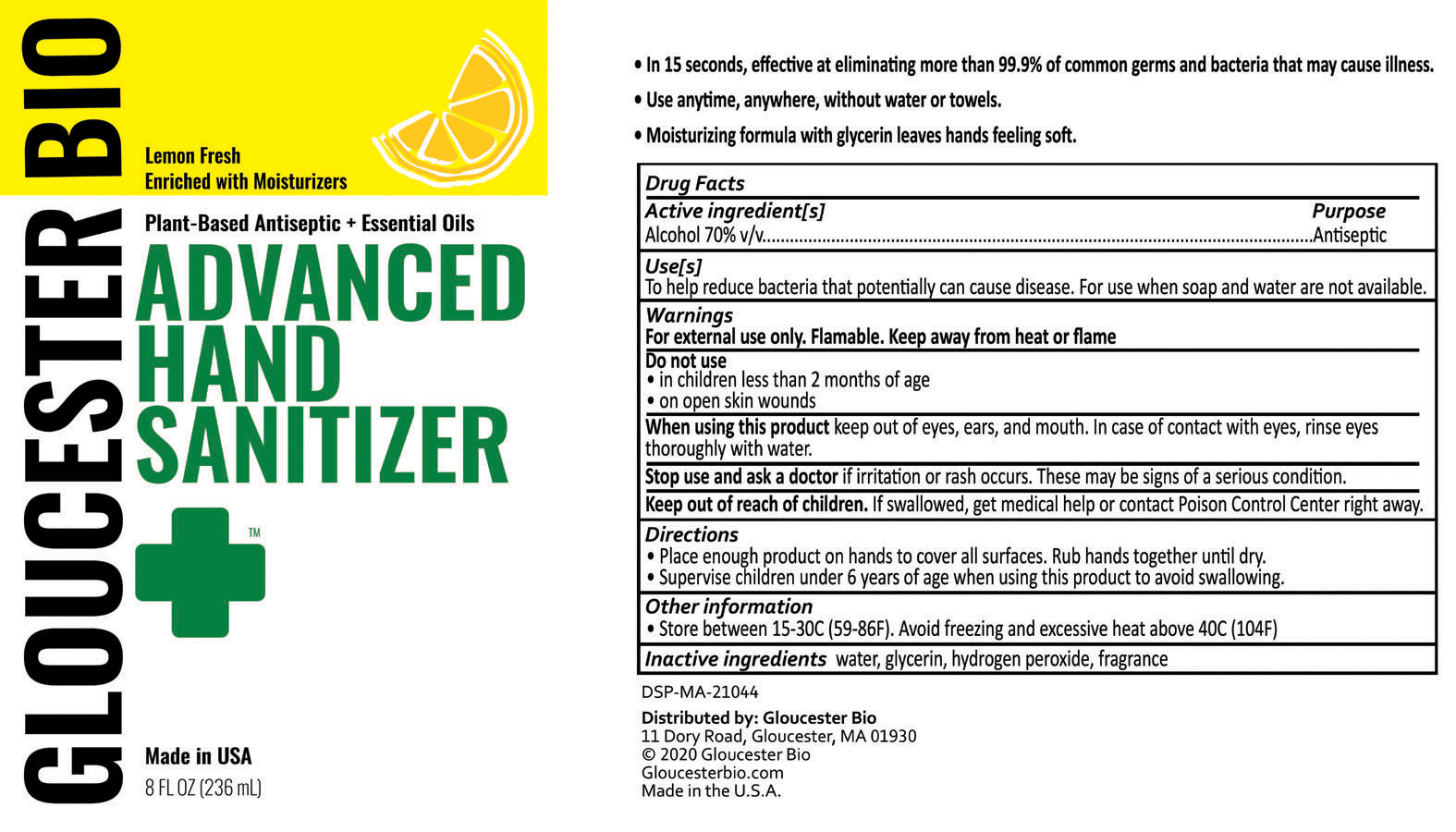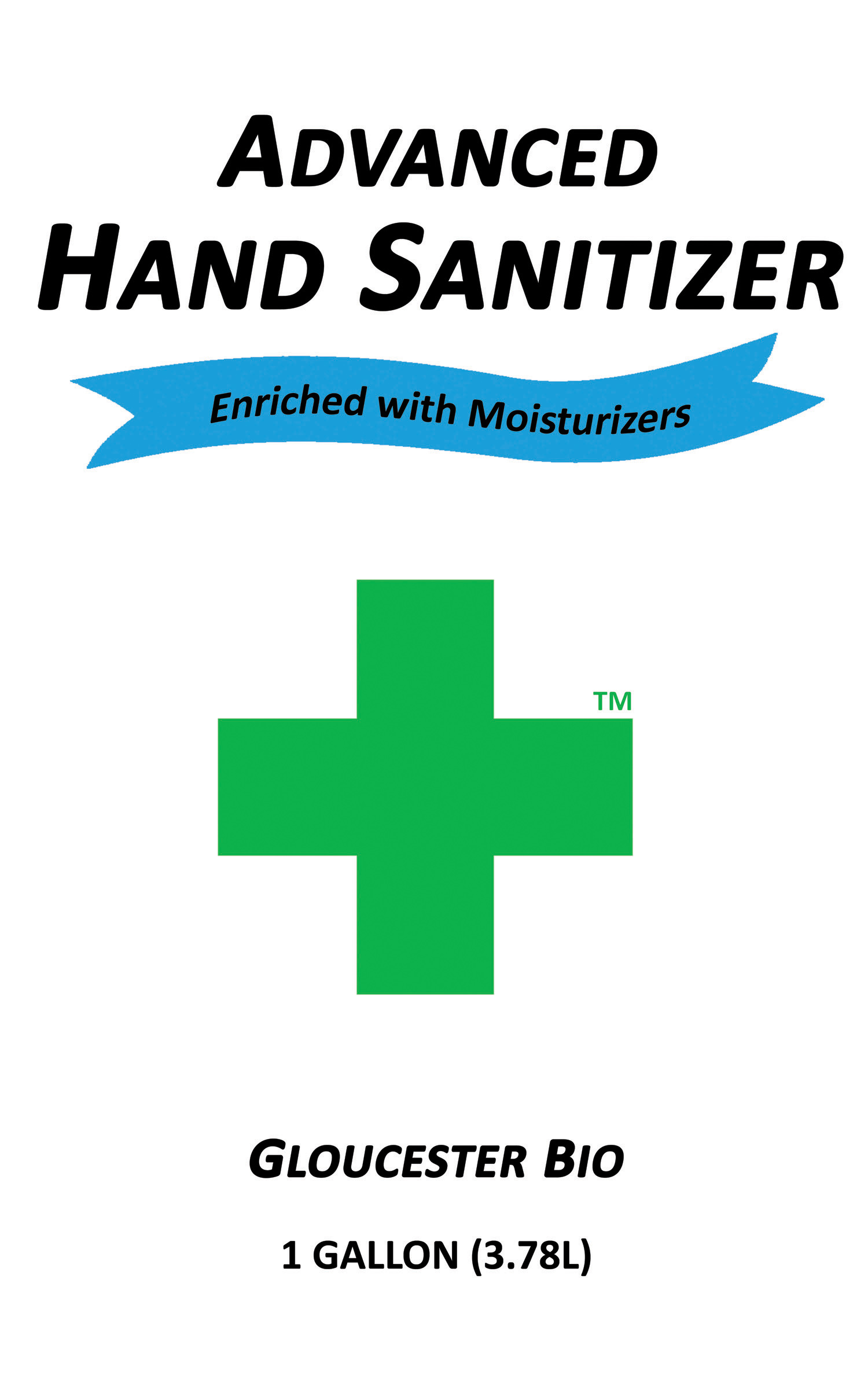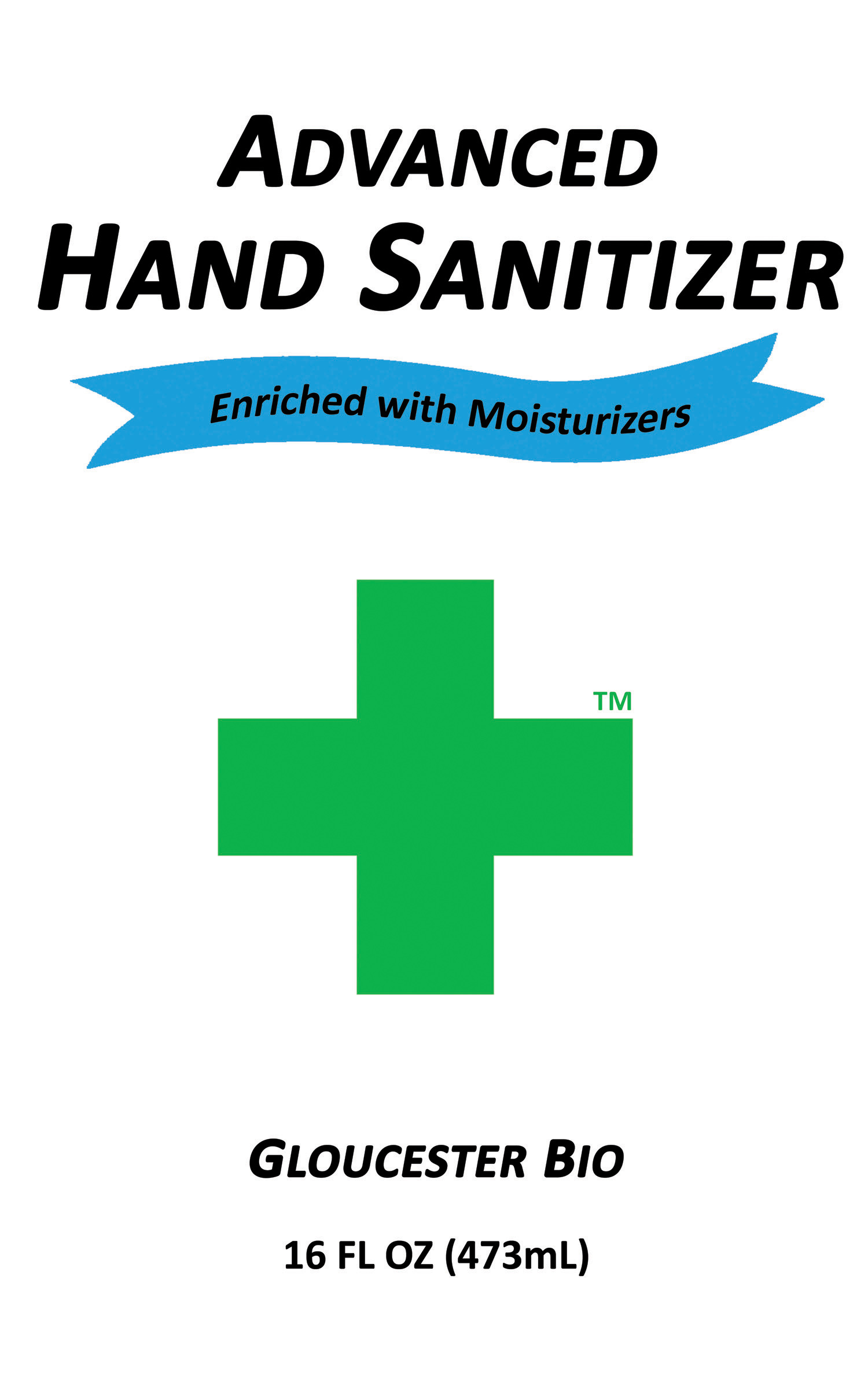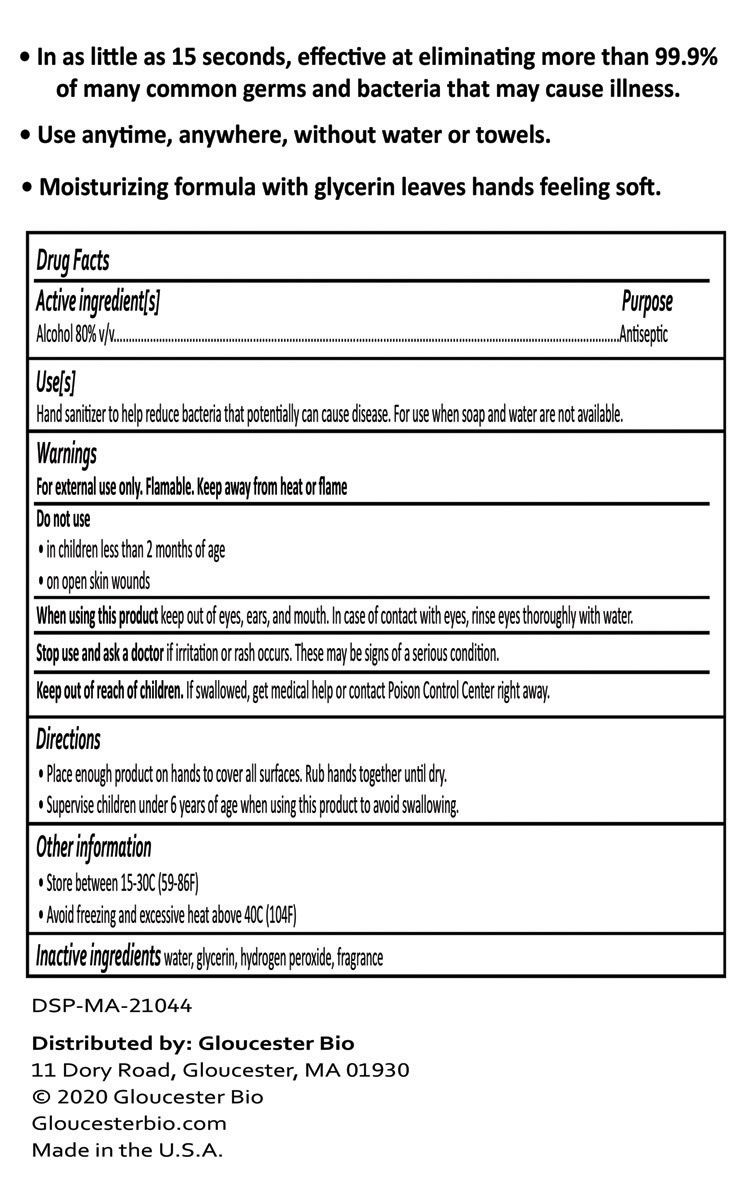 DRUG LABEL: Hand Sanitizer
NDC: 74128-070 | Form: SPRAY
Manufacturer: Tekkware, Inc. d.b.a. Gloucester Bio
Category: otc | Type: HUMAN OTC DRUG LABEL
Date: 20200612

ACTIVE INGREDIENTS: ALCOHOL 70 mL/100 mL
INACTIVE INGREDIENTS: WATER; GLYCERIN; LEMON OIL

Alcohol (Ethyl Alcohol or Ethanol)

Ethyl Alcohol

Hand Sanitizer

OTC Antiseptic Drug Products

Inactive Ingredients

water, glycerin, hydrogen peroxide, fragrance

Uses

Hand sanitizer to help reduce bacteria that can potentially cause disease. For use when soap and water are not available.

Keep out of reach of children

If swallowed, get medical help or contact Poison Control Center right away.

Directions

- Place enough product on hands to cover all surfaces. Rub hands together until dry.

- Supervise children under six years of age when using this product to avoid swallowing.

Warnings

For external use only. Flammable. Keep away from heat or flame.

- Do not use in children less than 2 months of age. Do not use on open skin wounds.

- When using this product keep out of eyes, ears, and mouth. In case of contact with eyes, rinse eyes thoroughly with water.

- Stop use and ask a doctor if irritation or rash occur. These may be signs of a serious condition.

473mL NDC: 74128-080-16

GBDrugfacts16oz

3785mL NDC: 74128-080-01

GBDrugFacts1gal

236mL NDC: 74128-070-08

118mL NDC: 74128-070-04